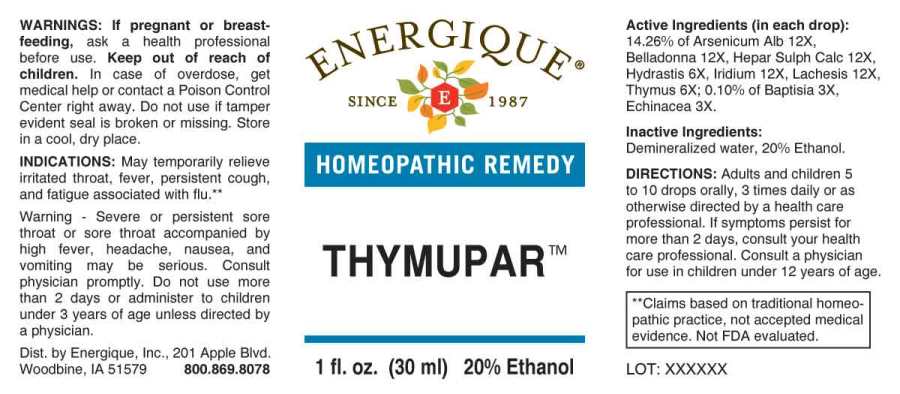 DRUG LABEL: Thymupar
NDC: 44911-0427 | Form: LIQUID
Manufacturer: Energique, Inc.
Category: homeopathic | Type: HUMAN OTC DRUG LABEL
Date: 20241030

ACTIVE INGREDIENTS: BAPTISIA TINCTORIA ROOT 3 [hp_X]/1 mL; ECHINACEA ANGUSTIFOLIA WHOLE 3 [hp_X]/1 mL; GOLDENSEAL 6 [hp_X]/1 mL; SUS SCROFA THYMUS 6 [hp_X]/1 mL; ARSENIC TRIOXIDE 12 [hp_X]/1 mL; ATROPA BELLADONNA WHOLE 12 [hp_X]/1 mL; CALCIUM SULFIDE 12 [hp_X]/1 mL; IRIDIUM 12 [hp_X]/1 mL; LACHESIS MUTA VENOM 12 [hp_X]/1 mL
INACTIVE INGREDIENTS: WATER; ALCOHOL

DRUG FACTS:

ACTIVE INGREDIENTS:

Baptisia Tinctoria 3X, Echinacea (Angustifolia) 3X, Hydrastis Canadensis 6X, Thymus (Suis) 6X, Arsenicum Album 12X, Belladonna 12X, Hepar Sulphuris Calcareum 12X, Iridium Metallicum 12X, Lachesis Mutus 12X.

INDICATIONS:

For temporary relieve irritated throat, fever, persistent cough, fatigue associated with flu. **

**Claims based on traditional homeopathic practice, not accepted medical evidence. Not FDA evaluated.

WARNINGS:

If pregnant or breast-feeding, ask a health professional before use.

Keep out of reach of children. In case of overdose, get medical help or contact a Poison Control Center right away.

Do not use if tamper evident seal is broken or missing. Store in a cool, dry place.

Warning: Severe or persistent sore throat or sore throat accompanied by high fever, headache, nausea, and vomiting may be serious. Consult physician promptly. Do not use more than 2 days or administer to children under 3 years of age unless directed by a physician.

Keep out of reach of children. In case of overdose, get medical help or contact a Poison Control Center right away.

DIRECTIONS:

Adults and children 5 to 10 drops orally, 3 times daily or as otherwise directed by a health care professional. If symptoms persist, consult your health care professional. Consult a physician for use in children under 12 years of age.

INDICATIONS:

For temporary relief of irritated throat, fever, persistent cough, fatigue associated with flu. **

**Claims based on traditional homeopathic practice, not accepted medical evidence. Not FDA evaluated.

INACTIVE INGREDIENTS:

Demineralized water, 20% Ethanol.

QUESTIONS:

Dist. by Energique, Inc., 201 Apple Blvd

Woodbine, IA 51579 800-869-8078

PACKAGE LABEL DISPLAY:

ENERGIQUE

SINCE 1987

HOMEOPATHIC REMEDY

THYMUPAR

1 fl. oz. (30 ml)